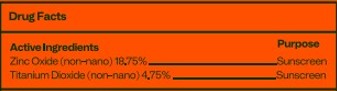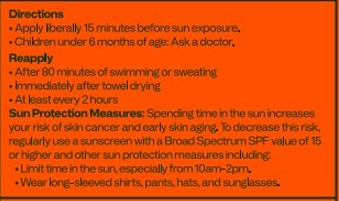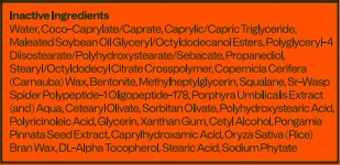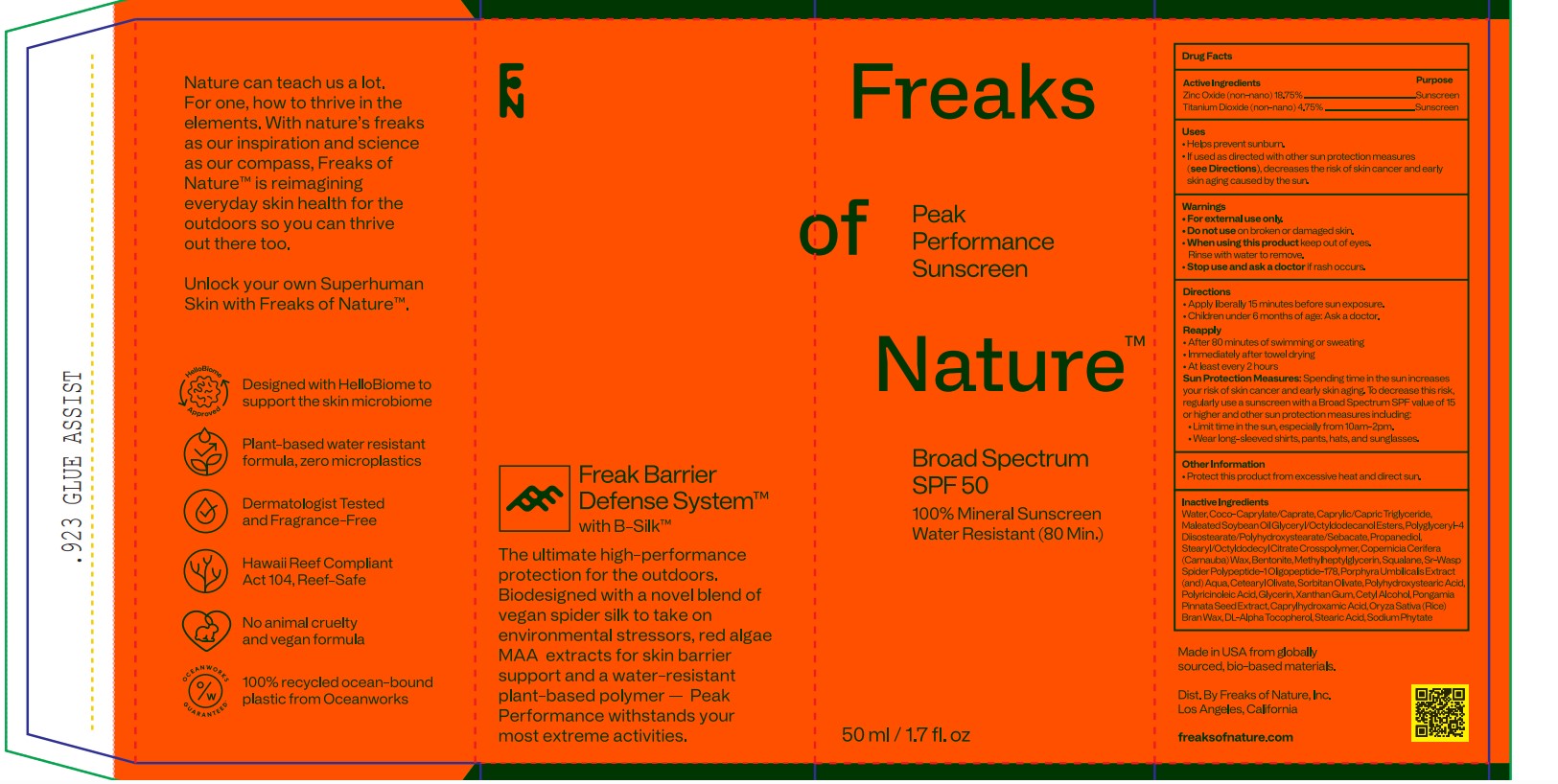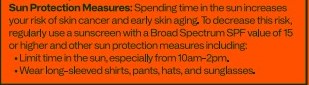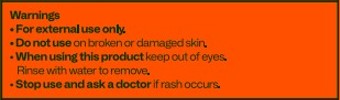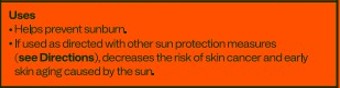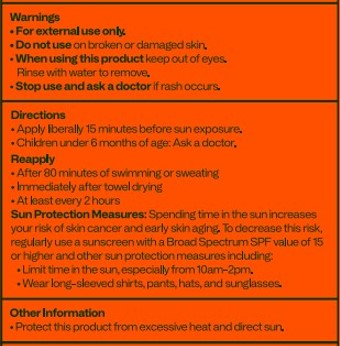 DRUG LABEL: Freaks of Nature Peak Performance SPF50
NDC: 57577-106 | Form: LOTION
Manufacturer: Milbar Laboratories
Category: otc | Type: HUMAN OTC DRUG LABEL
Date: 20240830

ACTIVE INGREDIENTS: ZINC OXIDE 11.025 g/50 mL; TITANIUM DIOXIDE 2.793 g/50 mL
INACTIVE INGREDIENTS: MEDIUM-CHAIN TRIGLYCERIDES; PROPANEDIOL; STEARYL/OCTYLDODECYL CITRATE CROSSPOLYMER; SQUALANE; WATER; SOYBEAN OIL GLYCERETH-8 ESTERS; POLYGLYCERYL-4 DIISOSTEARATE/POLYHYDROXYSTEARATE/SEBACATE; RICE BRAN; .ALPHA.-TOCOPHEROL, DL-; STEARIC ACID; CETEARYL OLIVATE; BENTONITE; PORPHYRA UMBILICALIS; POLYGLYCEROL POLYRICINOLEIC ACID; PHYTATE SODIUM; CAPRYLHYDROXAMIC ACID; CARNAUBA WAX; POLYHYDROXYSTEARIC ACID (2300 MW); XANTHAN GUM; GLYCERIN; AMINO ACIDS, SILK; SORBITAN OLIVATE; PONGAMIA PINNATA SEED; CETYL ALCOHOL; COCO-CAPRYLATE/CAPRATE; CAPRYLYL GLYCOL

Squared Circles / Freaks of Nature Peak Performance SPF 50 Lotion